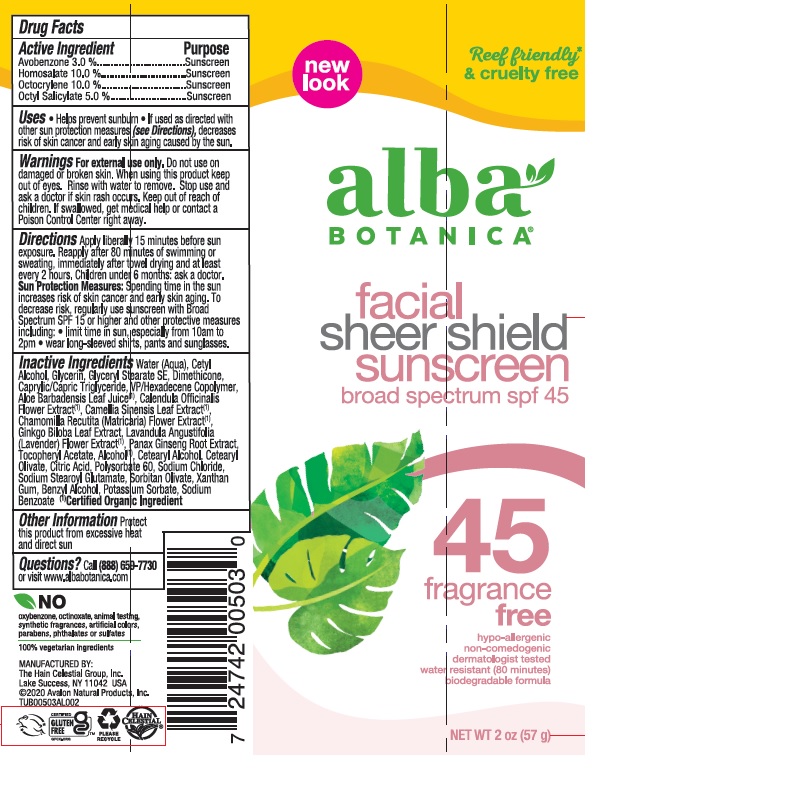 DRUG LABEL: Facial Sheer Shield SPF45
NDC: 61995-1969 | Form: LOTION
Manufacturer: The Hain Celestial Group, Inc.
Category: otc | Type: HUMAN OTC DRUG LABEL
Date: 20221201

ACTIVE INGREDIENTS: AVOBENZONE 3 g/100 g; HOMOSALATE 10 g/100 g; OCTISALATE 5 g/100 g; OCTOCRYLENE 10 g/100 g
INACTIVE INGREDIENTS: GLYCERYL STEARATE SE; ORANGE OIL; CALENDULA OFFICINALIS FLOWER; GINKGO BILOBA LEAF OIL; .ALPHA.-TOCOPHEROL ACETATE; CETEARYL OLIVATE; ANHYDROUS CITRIC ACID; POLYSORBATE 60; SODIUM STEAROYL GLUTAMATE; SORBITAN OLIVATE; ALCOHOL; CHAMOMILE; LAVANDULA ANGUSTIFOLIA FLOWERING TOP; CETOSTEARYL ALCOHOL; SODIUM CHLORIDE; VINYLPYRROLIDONE/HEXADECENE COPOLYMER; ALOE VERA LEAF; GREEN TEA LEAF; CAPRYLIC/CAPRIC ACID; PANAX GINSENG ROOT OIL; CETYL ALCOHOL; GLYCERIN; POTASSIUM SORBATE; SODIUM BENZOATE; XANTHAN GUM; BENZYL ALCOHOL; DIMETHICONE; WATER

AL00969 Sweet Pea Sheer Shield SPF 45

Active Ingredients

Avobenzone - 3.0%

Homosalate – 10.0%

Octocrylene – 10.0%

Octyl Salicylate – 5.0%

DOSAGE AND ADMINISTRATION

Apply liberally 15 minutes before sun exposure. Reapply after 80 minutes of swimming or sweating, immediately after towel drying and at least every 2 hours.

PURPOSE

Sunscreen

WARNINGS

For external use only. Do not use on damaged or broken skin. When using this product keep out of eyes. Rinse with water to remove. Stop use and ask a doctor if skin rash occurs. Keep out of reach of children. If swallowed, get medical help or contact a Poison Control Center right away.

Keep out of reach of children.

INACTIVE INGREDIENT

Water (Aqua), Cetyl Alcohol, Glycerin, Glyceryl Stearate SE, Dimethicone, Caprylic/Capric Triglyceride, VP/Hexadecene Copolymer, Aloe Barbadensis Leaf Juice(1), Calendula Officinalis Flower Extract(1), Camellia Sinensis Leaf Extract(1), Chamomilla Recutita (Matricaria) Flower Extract(1), Ginkgo Biloba Leaf Extract, Lavandula Angustifolia (Lavender) Flower Extract(1), Panax Ginseng Root Extract, Tocopheryl Acetate, Alcohol(1), Cetearyl Alcohol, Cetearyl Olivate, Citric Acid, Polysorbate 60, Sodium Chloride, Sodium Stearoyl Glutamate, Sorbitan Olivate, Xanthan Gum, Benzyl Alcohol, Potassium Sorbate, Sodium Benzoate.

(1) Certified Organic Ingredient

INDICATIONS AND USAGE

Helps prevent sunburn

If used as directed with other sun protection measures (see Directions) decreases risk of skin cancer and early signs of agin caused by the sun.

RECENT MAJOR CHANGES

Indications and Usage update

Inactive ingredients update